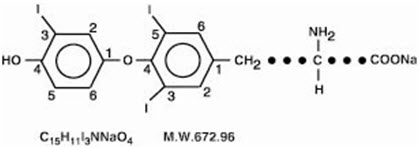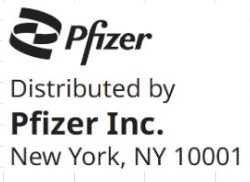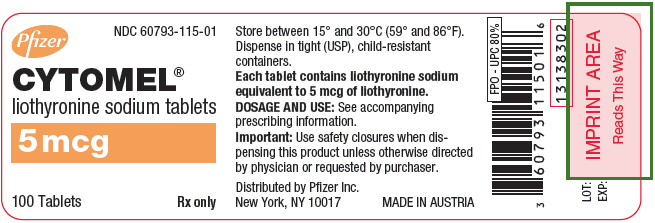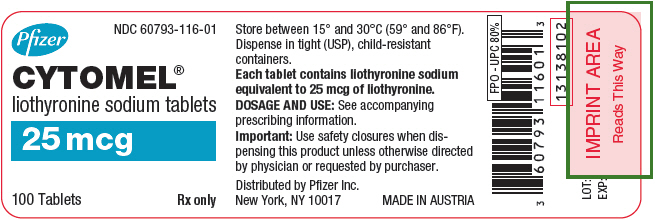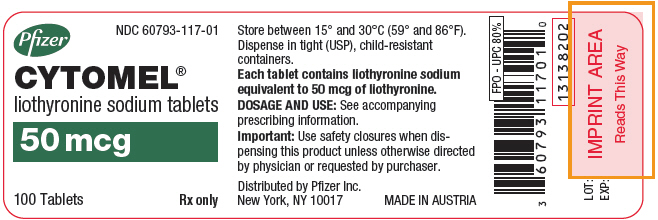 DRUG LABEL: Cytomel
NDC: 60793-115 | Form: TABLET
Manufacturer: Pfizer Laboratories Div Pfizer Inc
Category: prescription | Type: HUMAN PRESCRIPTION DRUG LABEL
Date: 20250404

ACTIVE INGREDIENTS: LIOTHYRONINE SODIUM 5 ug/1 1

HIGHLIGHTS OF PRESCRIBING INFORMATION

These highlights do not include all the information needed to use CYTOMEL safely and effectively. See full prescribing information for CYTOMEL.
CYTOMEL® (liothyronine sodium) tablets, for oral use
Initial U.S. Approval: 1956

WARNING: NOT FOR TREATMENT OF OBESITY OR FOR WEIGHT LOSS

See full prescribing information for complete boxed warning.

- Thyroid hormones, including CYTOMEL, should not be used for the treatment of obesity or for weight loss.
- Doses beyond the range of daily hormonal requirements may produce serious or even life-threatening manifestations of toxicity (6, 7.7, 10).

1 INDICATIONS AND USAGE

CYTOMEL is an L-triiodothyronine (T3) indicated for:

- Hypothyroidism: As replacement in primary (thyroidal), secondary (pituitary), and tertiary (hypothalamic) congenital or acquired hypothyroidism (1.1)
- Pituitary Thyroid-Stimulating Hormone (TSH) Suppression: As an adjunct to surgery and radioiodine therapy in the management of well-differentiated thyroid cancer (1.2)
- Thyroid Suppression Test: As a diagnostic agent in suppression tests to differentiate suspected mild hyperthyroidism or thyroid gland autonomy (1.3)

Limitations of Use:

- Not indicated for suppression of benign thyroid nodules and nontoxic diffuse goiter in iodine-sufficient patients. (1)
- Not indicated for treatment of hypothyroidism during the recovery phase of subacute thyroiditis. (1)

2 DOSAGE AND ADMINISTRATION

- Administer CYTOMEL orally once daily and individual dosage according to patient response and laboratory findings (2.1)
- See full prescribing information for recommended dosage for hypothyroidism (2.2) TSH suppression in well-differentiated thyroid cancer (2.3) and for thyroid suppression test (2.4)
- When switching a patient to CYTOMEL, discontinue levothyroxine therapy and initiate CYTOMEL at a low dosage. Gradually increase the dose according to the patient's response (2.5)
- Adequacy of therapy determined with periodic monitoring of TSH and T3 levels as well as clinical status (2.6)

3 DOSAGE FORMS AND STRENGTHS

Tablets: 5 mcg, 25 mcg, 50 mcg (3)

4 CONTRAINDICATIONS

Uncorrected adrenal cortical insufficiency (4)

5 WARNINGS AND PRECAUTIONS

- Cardiac adverse reactions in the elderly and in patients with underlying cardiovascular disease: Initiate CYTOMEL at less than the full replacement dose because of the increased risk of cardiac adverse reactions, including atrial fibrillation (2.3, 5.1, 8.5)
- Myxedema coma: Do not use oral thyroid hormone drug products to treat myxedema coma. (5.2)
- Acute adrenal crisis in patients with concomitant adrenal insufficiency: Treat with replacement glucocorticoids prior to initiation of CYTOMEL treatment (5.3)
- Prevention of hyperthyroidism or incomplete treatment of hypothyroidism: Proper dose titration and careful monitoring is critical to prevent the persistence of hypothyroidism or the development of hyperthyroidism. (5.4)
- Worsening of diabetic control: Therapy in patients with diabetes mellitus may worsen glycemic control and result in increased antidiabetic agent or insulin requirements. Carefully monitor glycemic control after starting, changing, or discontinuing thyroid hormone therapy (5.5)
- Decreased bone mineral density associated with thyroid hormone over-replacement: Over-replacement can increase bone resorption and decrease bone mineral density. Give the lowest effective dose (5.6)

6 ADVERSE REACTIONS

Most common adverse reactions for CYTOMEL are primarily those of hyperthyroidism due to therapeutic overdosage: arrhythmias, myocardial infarction, dyspnea, headache, nervousness, irritability, insomnia, tremors, muscle weakness, increased appetite, weight loss, diarrhea, heat intolerance, menstrual irregularities, and skin rash (6)

To report SUSPECTED ADVERSE REACTIONS, contact Pfizer, Inc. at 1-800-438-1985 or FDA at 1-800-FDA-1088 or www.fda.gov/medwatch.

7 DRUG INTERACTIONS

See full prescribing information for drugs that affect thyroid hormone pharmacokinetics and metabolism (e.g., absorption, synthesis, secretion, catabolism, protein binding, and target tissue response) and may alter the therapeutic response to CYTOMEL (7)

8 USE IN SPECIFIC POPULATIONS

Pregnancy may require the use of higher doses of thyroid hormone (2.2, 8.1)

FULL PRESCRIBING INFORMATION

WARNING: NOT FOR TREATMENT OF OBESITY OR FOR WEIGHT LOSS

- Thyroid hormones, including CYTOMEL, either alone or with other therapeutic agents, should not be used for the treatment of obesity or for weight loss.
- In euthyroid patients, doses within the range of daily hormonal requirements are ineffective for weight reduction.
- Larger doses may produce serious or even life-threatening manifestations of toxicity, particularly when given in association with sympathomimetic amines such as those used for their anorectic effects [see Adverse Reactions (6), Drug Interactions (7.7), and Overdosage (10)].

1 INDICATIONS AND USAGE

1.1 Hypothyroidism

CYTOMEL is indicated as a replacement therapy in primary (thyroidal), secondary (pituitary), and tertiary (hypothalamic) congenital or acquired hypothyroidism.

1.2 Pituitary Thyroid-Stimulating Hormone (TSH) Suppression

CYTOMEL is indicated as an adjunct to surgery and radioiodine therapy in the management of well-differentiated thyroid cancer.

1.3 Thyroid Suppression Test

CYTOMEL is indicated as a diagnostic agent in suppression tests to differentiate suspected mild hyperthyroidism or thyroid gland autonomy.

Limitations of Use

- CYTOMEL is not indicated for suppression of benign thyroid nodules and nontoxic diffuse goiter in iodine-sufficient patients as there are no clinical benefits and overtreatment with CYTOMEL may induce hyperthyroidism [see Warnings and Precautions (5.4)].
- CYTOMEL is not indicated for treatment of hypothyroidism during the recovery phase of subacute thyroiditis.

2 DOSAGE AND ADMINISTRATION

2.1 General Principles of Dosing

The dose of CYTOMEL for hypothyroidism or pituitary TSH suppression depends on a variety of factors including: the patient's age, body weight, cardiovascular status, concomitant medical conditions (including pregnancy), concomitant medications, co-administered food and the specific nature of the condition being treated [see Dosage and Administration (2.2, 2.3, 2.4), Warnings and Precautions (5), and Drug Interactions (7)]. Dosing must be individualized to account for these factors and dose adjustments made based on periodic assessment of the patient's clinical response and laboratory parameters [see Dosage and Administration (2.4)].

Administer CYTOMEL tablets orally once daily.

2.2 Recommended Dosage for Hypothyroidism

Adults

The recommended starting dosage is 25 mcg orally once daily. Increase the dose by 25 mcg daily every 1 or 2 weeks, if needed. The usual maintenance dose is 25 mcg to 75 mcg once daily.

For elderly patients or patients with underlying cardiac disease, start with CYTOMEL 5 mcg once daily and increase by 5 mcg increments at the recommended intervals.

Serum TSH is not a reliable measure of CYTOMEL dose adequacy in patients with secondary or tertiary hypothyroidism and should not be used to monitor therapy. Use the serum T3 level to monitor adequacy of therapy in this patient population.

Pediatric Patients

The recommended starting dosage is 5 mcg once daily, with a 5 mcg increase every 3 to 4 days until the desired response is achieved. Infants a few months old may require 20 mcg once daily for maintenance. At 1 year of age, 50 mcg once daily may be required. Above 3 years of age, the full adult dosage may be necessary [see Use in Specific Populations (8.4)].

Newborns (0 to 3 months) at Risk for Cardiac Failure:

Consider a lower starting dose in infants at risk for cardiac failure. Increase the dose as needed based on clinical and laboratory response.

Pediatric Patients at Risk for Hyperactivity:

To minimize the risk of hyperactivity in pediatric patients, start at one-fourth the recommended full replacement dose, and increase on a weekly basis by one-fourth the full recommended replacement dose until the full recommended replacement dose is reached.

Pregnancy

Pre-existing Hypothyroidism: Thyroid hormone dose requirements may increase during pregnancy. Measure serum TSH and free-T4 as soon as pregnancy is confirmed and, at minimum, during each trimester of pregnancy. In patients with primary hypothyroidism, maintain serum TSH in the trimester-specific reference range. For patients with serum TSH above the normal trimester-specific range, increase the dose of thyroid hormone and measure TSH every 4 weeks until a stable dose is reached and serum TSH is within the normal trimester-specific range. Reduce thyroid hormone dosage to pre-pregnancy levels immediately after delivery and measure serum TSH levels 4 to 8 weeks postpartum to ensure thyroid hormone dose is appropriate.

2.3 Recommended Dosage for TSH Suppression in Well-Differentiated Thyroid Cancer

The dose of CYTOMEL should target TSH levels within the desired therapeutic range. This may require higher doses, depending on the target level for TSH suppression.

2.4 Recommended Dosage for Thyroid Suppression Test

The recommended dose is 75 mcg to 100 mcg daily for 7 days, with radioactive iodine uptake being determined before and after the 7 day administration of CYTOMEL. If thyroid function is normal, the radioiodine uptake will drop significantly after treatment. A 50% or greater suppression of uptake indicates a normal thyroid-pituitary axis.

2.5 Switching from Levothyroxine to CYTOMEL

CYTOMEL has a rapid onset of action and residual effects of the other thyroid preparation may persist for the first several weeks after initiating CYTOMEL therapy. When switching a patient to CYTOMEL, discontinue levothyroxine therapy and initiate CYTOMEL at a low dosage. Gradually increase the CYTOMEL dose according to the patient's response.

2.6 Monitoring TSH and Triiodothyronine (T3) Levels

Assess the adequacy of therapy by periodic assessment of laboratory tests and clinical evaluation. Persistent clinical and laboratory evidence of hypothyroidism despite an apparent adequate replacement dose of CYTOMEL may be evidence of inadequate absorption, poor compliance, drug interactions, or a combination of these factors.

Adults

In adult patients with primary hypothyroidism, monitor serum TSH periodically after initiation of the therapy or any change in dose. To check the immediate response to therapy before the TSH has had a chance to respond or if your patient's status needs to be assessed prior to that point, measurement of total T3 would be most appropriate. In patients on a stable and appropriate replacement dose, evaluate clinical and biochemical response every 6 to 12 months and whenever there is a change in the patient's clinical status.

Pediatrics

In pediatric patients with hypothyroidism, assess the adequacy of replacement therapy by measuring serum TSH and T3 levels. For pediatric patients three years of age and older, the recommended monitoring is every 3 to 12 months thereafter, following dose stabilization until growth and puberty are completed. Poor compliance or abnormal values may necessitate more frequent monitoring. Perform routine clinical examination, including assessment of development, mental and physical growth, and bone maturation, at regular intervals.

While the general aim of therapy is to normalize the serum TSH level, TSH may not normalize in some patients due to in utero hypothyroidism causing a resetting of pituitary-thyroid feedback. Failure of the serum TSH to decrease below 20 IU per liter after initiation of CYTOMEL therapy may indicate the child is not receiving adequate therapy. Assess compliance, dose of medication administered, and method of administration prior to increasing the dose of CYTOMEL [see Warnings and Precautions (5.1) and Use in Specific Populations (8.4)].

Secondary and Tertiary Hypothyroidism

Monitor serum T3 levels and maintain in the normal range.

3 DOSAGE FORMS AND STRENGTHS

Tablets (round, white to off-white) available as follows:

- 5 mcg: debossed with KPI on one side and 115 on the other side
- 25 mcg: scored on one side and debossed with KPI and 116 on the other side
- 50 mcg: scored on one side and debossed with KPI and 117 on the other side

4 CONTRAINDICATIONS

CYTOMEL is contraindicated in patients with uncorrected adrenal insufficiency [see Warnings and Precautions (5.3)].

5 WARNINGS AND PRECAUTIONS

5.1 Cardiac Adverse Reactions in the Elderly and in Patients with Underlying Cardiovascular Disease

Overtreatment with thyroid hormone may cause an increase in heart rate, cardiac wall thickness, and cardiac contractility and may precipitate angina or arrhythmias, particularly in patients with cardiovascular disease and in elderly patients. Initiate CYTOMEL therapy in this population at lower doses than those recommended in younger individuals or in patients without cardiac disease [see Dosage and Administration (2.3) and Use in Specific Populations (8.5)].

Monitor for cardiac arrhythmias during surgical procedures in patients with coronary artery disease receiving suppressive CYTOMEL therapy. Monitor patients receiving concomitant CYTOMEL and sympathomimetic agents for signs and symptoms of coronary insufficiency. If cardiovascular symptoms develop or worsen, reduce or withhold the CYTOMEL dose for one week and restart at a lower dose.

5.2 Myxedema Coma

Myxedema coma is a life-threatening emergency characterized by poor circulation and hypometabolism, and may result in unpredictable absorption of thyroid hormone from the gastrointestinal tract. Use of oral thyroid hormone drug products is not recommended to treat myxedema coma. Administer thyroid hormone products formulated for intravenous administration to treat myxedema coma.

5.3 Acute Adrenal Crisis in Patients with Concomitant Adrenal Insufficiency

Thyroid hormone increases metabolic clearance of glucocorticoids. Initiation of thyroid hormone therapy prior to initiating glucocorticoid therapy may precipitate an acute adrenal crisis in patients with adrenal insufficiency. Treat patients with adrenal insufficiency with replacement glucocorticoids prior to initiating treatment with CYTOMEL [see Contraindications (4)].

5.4 Prevention of Hyperthyroidism or Incomplete Treatment of Hypothyroidism

CYTOMEL has a narrow therapeutic index. Over- or undertreatment with CYTOMEL may have negative effects on growth and development, cardiovascular function, bone metabolism, reproductive function, cognitive function, emotional state, gastrointestinal function, and on glucose and lipid metabolism. Titrate the dose of CYTOMEL carefully and monitor response to titration to avoid these effects [see Dosage and Administration (2.4)]. Monitor for the presence of drug or food interactions when using CYTOMEL and adjust the dose as necessary [see Drug Interactions (7) and Clinical Pharmacology (12.3)].

5.5 Worsening of Diabetic Control

Addition of thyroid hormone therapy in patients with diabetes mellitus may worsen glycemic control and result in increased antidiabetic agent or insulin requirements. Carefully monitor glycemic control after starting, changing, or discontinuing CYTOMEL [see Drug Interactions (7.2)].

5.6 Decreased Bone Mineral Density Associated with Thyroid Hormone Over-Replacement

Increased bone resorption and decreased bone mineral density may occur as a result of thyroid hormone over-replacement, particularly in post-menopausal women. The increased bone resorption may be associated with increased serum levels and urinary excretion of calcium and phosphorous, elevations in bone alkaline phosphatase, and suppressed serum parathyroid hormone levels. Administer the minimum dose of CYTOMEL that achieves the desired clinical and biochemical response to mitigate against this risk.

6 ADVERSE REACTIONS

Adverse reactions associated with CYTOMEL therapy are primarily those of hyperthyroidism due to therapeutic overdosage [see Warnings and Precautions (5.4) and Overdosage (10)]. They include the following:

General: fatigue, increased appetite, weight loss, heat intolerance, fever, excessive sweating

Central nervous system: headache, hyperactivity, nervousness, anxiety, irritability, emotional lability, insomnia

Musculoskeletal: tremors, muscle weakness and cramps

Cardiovascular: palpitations, tachycardia, arrhythmias, increased pulse and blood pressure, heart failure, angina, myocardial infarction, cardiac arrest

Respiratory: dyspnea

Gastrointestinal: diarrhea, vomiting, abdominal cramps, elevations in liver function tests

Dermatologic: hair loss, flushing

Endocrine: decreased bone mineral density

Reproductive: menstrual irregularities, impaired fertility

Adverse Reactions in Pediatric Patients

Pseudotumor cerebri and slipped capital femoral epiphysis have been reported in pediatric patients receiving thyroid replacement therapy. Overtreatment may result in craniosynostosis in infants and premature closure of the epiphyses in pediatric patients with resultant compromised adult height.

Hypersensitivity Reactions

Hypersensitivity reactions to inactive ingredients have occurred in patients treated with thyroid hormone products. These include urticaria, pruritus, skin rash, flushing, angioedema, various gastrointestinal symptoms (abdominal pain, nausea, vomiting and diarrhea), fever, arthralgia, serum sickness and wheezing.

7 DRUG INTERACTIONS

7.1 Drugs Known to Affect Thyroid Hormone Pharmacokinetics

Many drugs can exert effects on thyroid hormone pharmacokinetics (e.g. absorption, synthesis, secretion, catabolism, protein binding, and target tissue response) and may alter the therapeutic response to CYTOMEL (see Tables 1 – 4).

Table 1: Drugs That May Decrease T3 Absorption (Hypothyroidism)
Potential impact: Concurrent use may reduce the efficacy of CYTOMEL by binding and delaying or preventing absorption, potentially resulting in hypothyroidism.
Drug or Drug Class | Effect
Bile Acid Sequestrants -Colesevelam -Cholestyramine -Colestipol Ion Exchange Resins -Kayexalate -Sevelamer | Bile acid sequestrants and ion exchange resins are known to decrease thyroid hormones absorption. Administer CYTOMEL at least 4 hours prior to these drugs or monitor TSH levels.

Table 2: Drugs That May Alter Triiodothyronine (T3) Serum Transport Without Affecting Free Thyroxine (FT4) Concentration (Euthyroidism)
Drug or Drug Class | Effect
Clofibrate Estrogen-containing oral contraceptives Estrogens (oral) Heroin / Methadone 5-Fluorouracil Mitotane Tamoxifen | These drugs may increase serum thyroxine-binding globulin (TBG) concentration.
Androgens / Anabolic Steroids Asparaginase Glucocorticoids Slow-Release Nicotinic Acid | These drugs may decrease serum TBG concentration.
Salicylates (>2 g/day) | Salicylates inhibit binding of T4 and T3 to TBG and transthyretin. An initial increase in serum FT4 is followed by return of FT4 to normal levels with sustained therapeutic serum salicylate concentrations, although total T4 levels may decrease by as much as 30%.
Other drugs: Carbamazepine Furosemide (>80 mg IV) Heparin Hydantoins Non-Steroidal Anti-inflammatory Drugs - Fenamates | These drugs may cause protein binding site displacement. Furosemide has been shown to inhibit the protein binding of T4 to TBG and albumin, causing an increased free-T4 fraction in serum. Furosemide competes for T4-binding sites on TBG, prealbumin, and albumin, so that a single high dose can acutely lower the total T4 level. Phenytoin and carbamazepine reduce serum protein binding of thyroid hormones, and total and FT4 may be reduced by 20% to 40%, but most patients have normal serum TSH levels and are clinically euthyroid. Closely monitor thyroid hormone parameters.

Table 3: Drugs That May Alter Hepatic Metabolism of Thyroid hormones
Potential impact: Stimulation of hepatic microsomal drug-metabolizing enzyme activity may cause increased hepatic degradation of thyroid hormones, resulting in increased CYTOMEL requirements.
Drug or Drug Class | Effect
Phenobarbital Rifampin | Phenobarbital has been shown to reduce the response to thyroxine. Phenobarbital increases L-thyroxine metabolism by inducing uridine 5'-diphospho-glucuronosyltransferase (UGT) and leads to a lower T4 serum levels. Changes in thyroid status may occur if barbiturates are added or withdrawn from patients being treated for hypothyroidism. Rifampin has been shown to accelerate the metabolism of thyroid hormones.

Table 4: Drugs That May Decrease Conversion of T4 to T3
Potential impact: Administration of these enzyme inhibitors decreases the peripheral conversion of T4 to T3, leading to decreased T3 levels. However, serum T4 levels are usually normal but may occasionally be slightly increased.
Drug or Drug Class | Effect
Beta-adrenergic antagonists (e.g., Propranolol >160 mg/day) | In patients treated with large doses of propranolol (>160 mg/day), T3 and T4 levels change, TSH levels remain normal, and patients are clinically euthyroid. Actions of particular beta-adrenergic antagonists may be impaired when a hypothyroid patient is converted to the euthyroid state.
Glucocorticoids (e.g., Dexamethasone ≥4 mg/day) | Short-term administration of large doses of glucocorticoids may decrease serum T3 concentrations by 30% with minimal change in serum T4 levels. However, long-term glucocorticoid therapy may result in slightly decreased T3 and T4 levels due to decreased TBG production (see above).
Other drugs: Amiodarone | Amiodarone inhibits peripheral conversion of levothyroxine (T4) to triiodothyronine (T3) and may cause isolated biochemical changes (increase in serum free-T4, and decreased or normal free-T3) in clinically euthyroid patients.

7.2 Antidiabetic Therapy

Addition of CYTOMEL therapy in patients with diabetes mellitus may worsen glycemic control and result in increased antidiabetic agent or insulin requirements. Carefully monitor glycemic control, especially when CYTOMEL is started, changed, or discontinued [see Warnings and Precautions (5.5)].

7.3 Oral Anticoagulants

CYTOMEL increases the response to oral anticoagulant therapy. Therefore, a decrease in the dose of anticoagulant may be warranted with correction of the hypothyroid state or when the CYTOMEL dose is increased. Closely monitor coagulation tests to permit appropriate and timely dosage adjustments.

7.4 Digitalis Glycosides

CYTOMEL may reduce the therapeutic effects of digitalis glycosides. Serum digitalis glycoside levels may be decreased when a hypothyroid patient becomes euthyroid, necessitating an increase in the dose of digitalis glycosides.

7.5 Antidepressant Therapy

Concurrent use of tricyclic (e.g., amitriptyline) or tetracyclic (e.g., maprotiline) antidepressants and CYTOMEL may increase the therapeutic and toxic effects of both drugs, possibly due to increased receptor sensitivity to catecholamines. Toxic effects may include increased risk of cardiac arrhythmias and central nervous system stimulation. CYTOMEL may accelerate the onset of action of tricyclics. Administration of sertraline in patients stabilized on CYTOMEL may result in increased CYTOMEL requirements.

7.6 Ketamine

Concurrent use of ketamine and CYTOMEL may produce marked hypertension and tachycardia. Closely monitor blood pressure and heart rate in these patients.

7.7 Sympathomimetics

Concurrent use of sympathomimetics and CYTOMEL may increase the effects of sympathomimetics or thyroid hormone. Thyroid hormones may increase the risk of coronary insufficiency when sympathomimetic agents are administered to patients with coronary artery disease.

7.8 Tyrosine-Kinase Inhibitors

Concurrent use of tyrosine-kinase inhibitors such as imatinib may cause hypothyroidism. Closely monitor TSH levels in such patients.

7.9 Drug-Laboratory Test Interactions

Consider changes in TBG concentration when interpreting T4 and T3 values. Measure and evaluate unbound (free) hormone in this circumstance. Pregnancy, infectious hepatitis, estrogens, estrogen-containing oral contraceptives, and acute intermittent porphyria increase TBG concentrations. Nephrosis, severe hypoproteinemia, severe liver disease, acromegaly, androgens and corticosteroids decrease TBG concentration. Familial hyper- or hypo-thyroxine binding globulinemias have been described, with the incidence of TBG deficiency approximating 1 in 9000.

8 USE IN SPECIFIC POPULATIONS

8.1 Pregnancy

Risk Summary

Experience with liothyronine use in pregnant women, including data from post-marketing studies, have not reported increased rates of major birth defects or miscarriages (see Data). There are risks to the mother and fetus associated with untreated hypothyroidism in pregnancy. Since TSH levels may increase during pregnancy, TSH should be monitored and CYTOMEL dosage adjusted during pregnancy (see Clinical Considerations). There are no animal studies conducted with liothyronine during pregnancy. CYTOMEL should not be discontinued during pregnancy and hypothyroidism diagnosed during pregnancy should be promptly treated.

The estimated background risk of major birth defects and miscarriage for the indicated population is unknown. In the U.S. general population, the estimated background risk of major birth defects and miscarriage in clinically recognized pregnancies is 2 to 4% and 15 to 20%, respectively.

Clinical Considerations

Disease-associated maternal and/or embryo/fetal risk

Maternal hypothyroidism during pregnancy is associated with a higher rate of complications, including spontaneous abortion, gestational hypertension, pre-eclampsia, stillbirth, and premature delivery. Untreated maternal hypothyroidism may have an adverse effect on fetal neurocognitive development.

Dose adjustments during pregnancy and the postpartum period

Pregnancy may increase CYTOMEL requirements. Serum TSH levels should be monitored and the CYTOMEL dosage adjusted during pregnancy. Since postpartum TSH levels are similar to preconception values, the CYTOMEL dosage should return to the pre-pregnancy dose immediately after delivery [see Dosage and Administration (2.3)].

Data

Human Data

Liothyronine is approved for use as a replacement therapy for hypothyroidism. Data from post-marketing studies have not reported increased rates of fetal malformations, miscarriages, or other adverse maternal or fetal outcomes associated with liothyronine use in pregnant women.

8.2 Lactation

Risk Summary

Limited published studies report that liothyronine is present in human milk. However, there is insufficient information to determine the effects of liothyronine on the breastfed infant and no available information on the effects of liothyronine on milk production. The developmental and health benefits of breastfeeding should be considered along with the mother's clinical need for CYTOMEL and any potential adverse effects on the breastfed infant from CYTOMEL or from the underlying maternal condition.

8.4 Pediatric Use

The initial dose of CYTOMEL varies with age and body weight. Dosing adjustments are based on an assessment of the individual patient's clinical and laboratory parameters [see Dosage and Administration (2.3, 2.4)].

In pediatric patients in whom a diagnosis of permanent hypothyroidism has not been established, discontinue thyroid hormone for a trial period, but only after the child is at least 3 years of age. Obtain serum TSH, T4, and T3 levels at the end of the trial period, and use laboratory test results and clinical assessments to guide diagnosis and treatment, if warranted [see Dosage and Administration (2.6)].

Congenital Hypothyroidism [see Dosage and Administration (2.2, 2.6)]

Rapid restoration of normal serum T4 concentrations is essential for preventing the adverse effects of congenital hypothyroidism on intellectual development as well as on overall physical growth and maturation. Therefore, initiate thyroid hormone immediately upon diagnosis. Thyroid hormone is generally continued for life in these patients.

Closely monitor infants during the first 2 weeks of thyroid hormone therapy for cardiac overload, arrhythmias, and aspiration from avid suckling.

Closely monitor patients to avoid undertreatment or overtreatment. Undertreatment may have deleterious effects on intellectual development and linear growth. Overtreatment is associated with craniosynostosis in infants, may adversely affect the tempo of brain maturation, and may accelerate the bone age and result in premature epiphyseal closure and compromised adult stature [see Dosage and Administration (2.6) and Adverse Reactions (6)].

Acquired Hypothyroidism in Pediatric Patients

Closely monitor patients to avoid undertreatment and overtreatment. Undertreatment may result in poor school performance due to impaired concentration and slowed mentation and in reduced adult height. Overtreatment may accelerate the bone age and result in premature epiphyseal closure and compromised adult stature.

Treated children may manifest a period of catch-up growth, which may be adequate in some cases to normalize adult height. In children with severe or prolonged hypothyroidism, catch-up growth may not be adequate to normalize adult height [see Adverse Reactions (6)].

8.5 Geriatric Use

Because of the increased prevalence of cardiovascular disease among the elderly, initiate CYTOMEL at less than the full replacement dose [see Dosage and Administration (2.3) and Warnings and Precautions (5.1)]. Atrial arrhythmias can occur in elderly patients. Atrial fibrillation is the most common of the arrhythmias observed with thyroid hormone overtreatment in the elderly.

10 OVERDOSAGE

The signs and symptoms of overdosage are those of hyperthyroidism [see Warnings and Precautions (5.4) and Adverse Reactions (6)]. In addition, confusion and disorientation may occur. Cerebral embolism, seizure, shock, coma, and death have been reported. Symptoms may not necessarily be evident or may not appear until several days after ingestion.

Reduce the CYTOMEL dose or temporarily discontinued if signs or symptoms of overdosage occur. Initiate appropriate supportive treatment as dictated by the patient's medical status.

For current information on the management of poisoning or overdosage, contact the National Poison Control Center at 1-800-222-1222 or www.poison.org.

11 DESCRIPTION

CYTOMEL tablets contain the active ingredient, liothyronine (L-triiodothyronine or LT3), a synthetic form of a thyroid hormone liothyronine in sodium salt form. It is chemically designated as L-Tyrosine, O-(4-hydroxy-3-iodophenyl)-3,5-diiodo-, monosodium salt. The molecular formula, molecular weight and structural formula of liothyronine sodium are given below.

CYTOMEL tablets contain liothyronine sodium equivalent to liothyronine in 5 mcg, 25 mcg, and 50 mcg. Inactive ingredients consist of calcium sulfate, corn starch, gelatin, stearic acid, sucrose and talc.

12 CLINICAL PHARMACOLOGY

12.1 Mechanism of Action

Thyroid hormones exert their physiologic actions through control of DNA transcription and protein synthesis. Triiodothyronine (T3) and L-thyroxine (T4) diffuse into the cell nucleus and bind to thyroid receptor proteins attached to DNA. This hormone nuclear receptor complex activates gene transcription and synthesis of messenger RNA and cytoplasmic proteins.

The physiological actions of thyroid hormones are produced predominantly by T3, the majority of which (approximately 80%) is derived from T4 by deiodination in peripheral tissues.

12.2 Pharmacodynamics

The onset of activity of liothyronine sodium occurs within a few hours. Maximum pharmacologic response occurs within 2 or 3 days.

12.3 Pharmacokinetics

Absorption

T3 is almost totally absorbed, 95 percent in 4 hours. The hormones contained in the natural preparations are absorbed in a manner similar to the synthetic hormones.

Distribution

Liothyronine sodium (T3) is not firmly bound to serum protein. The higher affinity of levothyroxine (T4) for both thyroid-binding globulin and thyroid-binding prealbumin as compared to triiodothyronine (T3) partially explains the higher serum levels and longer half-life of the former hormone. Both protein-bound hormones exist in reverse equilibrium with minute amounts of free hormone, the latter accounting for the metabolic activity.

Elimination

Metabolism

The major pathway of thyroid hormone metabolism is through sequential deiodination. Approximately 80% of circulating T3 is derived from peripheral T4 by monodeiodination. The liver is the major site of degradation for both T4 and T3. T3 is further deiodinated to diiodothyronine. Thyroid hormones are also metabolized via conjugation with glucuronides and sulfates and excreted directly into the bile and gut where they undergo enterohepatic recirculation.

Excretion

Thyroid hormones are primarily eliminated by the kidneys. A portion of the conjugated hormone reaches the colon unchanged and is eliminated in the feces. The biological half-life is about 2-1/2 days.

13 NONCLINICAL TOXICOLOGY

13.1 Carcinogenesis, Mutagenesis, Impairment of Fertility

Animal studies have not been performed to evaluate the carcinogenic potential, mutagenic potential or effects on fertility of liothyronine sodium.

16 HOW SUPPLIED/STORAGE AND HANDLING

CYTOMEL tablets (round, white to off-white) are supplied as follows:

Strength | Tablet Markings | NDC – bottles of 100
5 mcg | Debossed with KPI on one side and 115 on the other side | 60793-115-01
25 mcg | Scored on one side and debossed with KPI and 116 on the other side | 60793-116-01
50 mcg | Scored on one side and debossed with KPI and 117 on the other side | 60793-117-01

STORAGE AND HANDLING

Store between 15°C and 30°C (59°F and 86°F).

17 PATIENT COUNSELING INFORMATION

Dosing and Administration

- Instruct patients that CYTOMEL should only be taken as directed by their healthcare provider.
- Instruct patients to notify their healthcare provider should they become pregnant or breastfeeding or are thinking of becoming pregnant, while taking CYTOMEL.

Important Information

- Inform patients that the liothyronine in CYTOMEL is intended to replace a hormone that is normally produced by the thyroid gland. Generally replacement therapy is to be taken for life.
- Inform patients that CYTOMEL should not be used as a primary or adjunctive therapy in a weight control program.
- Instruct patients to notify their healthcare provider if they are taking any other medications, including prescription and over-the-counter preparations.
- Instruct patients to notify their healthcare provider of any other medical conditions, particularly heart disease, diabetes, clotting disorders, and adrenal or pituitary gland problems, as the dose of medications used to control these other conditions may need to be adjusted while taking CYTOMEL. If patents are taking anticoagulants (blood thinners), their clotting status should be checked frequently.
- Instruct patients to notify their physician or dentist if they are taking CYTOMEL prior to any surgery.

Adverse Reactions

- Instruct patients to notify their healthcare provider if they experience any of the following symptoms: rapid or irregular heartbeat, chest pain, shortness of breath, leg cramps, headache, nervousness, irritability, sleeplessness, tremors, change in appetite, weight gain or loss, vomiting, diarrhea, excessive sweating, heat intolerance, fever, changes in menstrual periods, hives or skin rash, or any other unusual medical event [see Adverse Reactions (6)].
- Inform patients that partial hair loss may occur rarely during the first few months of CYTOMEL therapy; this is usually temporary [see Adverse Reactions (6)].

This product's label may have been updated. For current full prescribing information, please visit www.pfizer.com.

LAB-0683-6.0

PRINCIPAL DISPLAY PANEL - 5 mcg Tablet Bottle Label

NDC 60793-115-01

Pfizer

CYTOMEL®
liothyronine sodium tablets

5 mcg

100 Tablets
Rx only

PRINCIPAL DISPLAY PANEL - 25 mcg Tablet Bottle Label

NDC 60793-116-01

Pfizer

CYTOMEL®
liothyronine sodium tablets

25 mcg

100 Tablets
Rx only

PRINCIPAL DISPLAY PANEL - 50 mcg Tablet Bottle Label

NDC 60793-117-01

Pfizer

CYTOMEL®
liothyronine sodium tablets

50 mcg

100 Tablets
Rx only